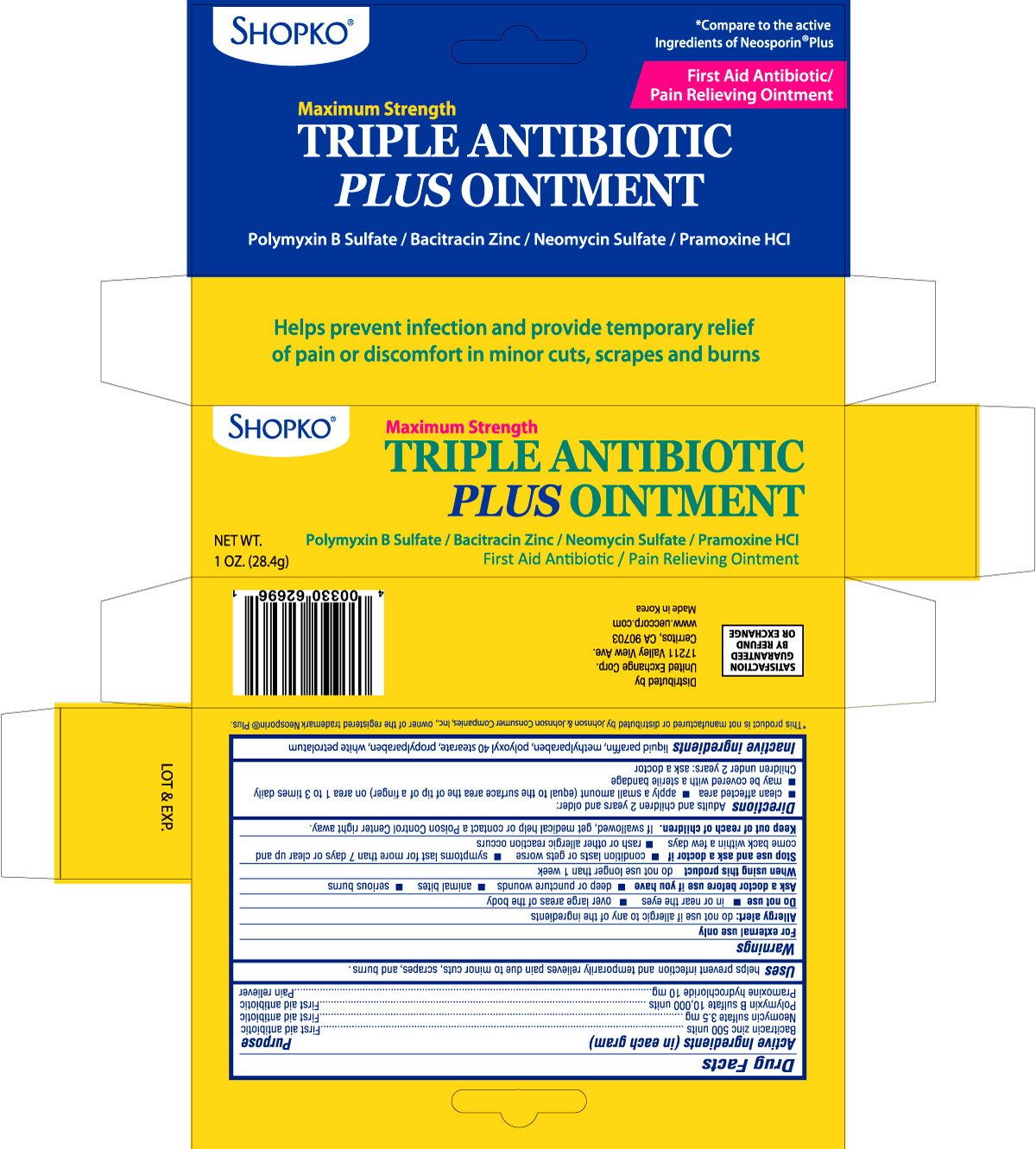 DRUG LABEL: SHOPKO TRIPLE ANTIBIOTIC PLUS
NDC: 55264-626 | Form: OINTMENT
Manufacturer: UNITED EXCHANGE CORP.
Category: otc | Type: HUMAN OTC DRUG LABEL
Date: 20110106

ACTIVE INGREDIENTS: BACITRACIN ZINC 500 [USP'U]/1 g; NEOMYCIN SULFATE 3.5 mg/1 g; POLYMYXIN B SULFATE 10000 [USP'U]/1 g; PRAMOXINE HYDROCHLORIDE 10 mg/1 g
INACTIVE INGREDIENTS: MINERAL OIL; METHYLPARABEN; POLYOXYL 40 STEARATE; PROPYLPARABEN; PETROLATUM

Drug Facts

Active Ingredients (in each gram) Purpose

Bacitracin zinc 500 units ............................................................................................First aid antibiotic

Neomycin sulfate 3.5mg .............................................................................................First aid antibiotic

Polymyxin B sulfate 10,000 units ................................................................................First aid antibiotic

Pramoxine hydrochloride 10mg ...................................................................................Pain reliever

Uses

helps prevent infection and temporarily relieves pain due to minor cuts, scrapes, and burns.

Warnings

For external use only

Allergy alert: do not use if allergic to any of the ingredients

Do not use

- in or near the eyes
- over large areas of the body

Ask a doctor before use if you have

- deep or puncture wounds
- animal bites
- serious burns

When using this product

do not use longer than 1 week

Stop use and ask a doctor if

- condition lasts or gets worse
- symptoms last for more than 7 days or clear up and come back within a few days
- rash or other allergic reaction occurs

Keep out of reach of children.

If swallowed, get medical help or contact a Poison Control Center right away.

Directions

Adults and children 2 years and older:

- clean affected area
- apply a small amount (equal to the surface area of the tip of a finger) on area 1 to 3 times daily

- may be covered with a sterile bandage

Children under 2 years: ask a doctor

Inactive ingredients

liquid paraffin, methylparaben, polyoxyl 40 stearate, propylparaben, white petrolatum

DOSAGE AND ADMINISTRATION

Distributed by

United Exchange Corp.

17211 Valley View Ave.

Cerritos, CA 90703

www.ueccorp.com

Made in Korea

PACKAGE LABEL

Enter section text here